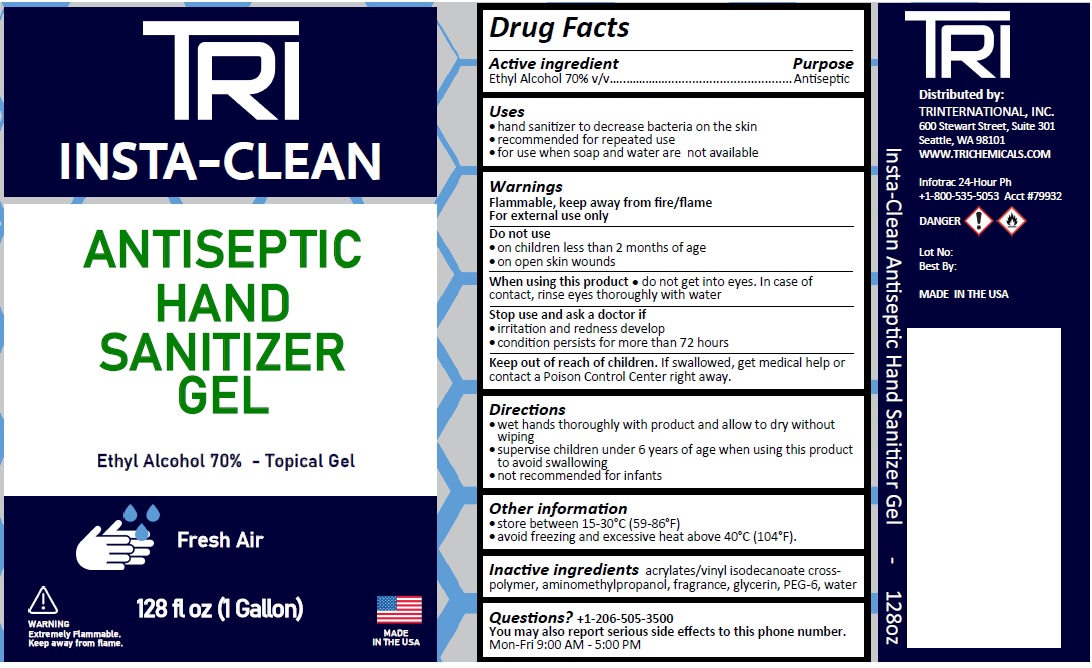 DRUG LABEL: Insta Clean Antiseptic Hand Sanitizer Gel Fresh Air
NDC: 79386-437 | Form: GEL
Manufacturer: Tr International Trading Company
Category: otc | Type: HUMAN OTC DRUG LABEL
Date: 20201107

ACTIVE INGREDIENTS: ALCOHOL 70 mL/100 mL
INACTIVE INGREDIENTS: ACRYLATES/VINYL ISODECANOATE CROSSPOLYMER (10000 MPA.S NEUTRALIZED AT 0.5%); AMINOMETHYLPROPANOL; GLYCERIN; POLYETHYLENE GLYCOL 300; WATER

TRI INSTA-CLEAN ANTISEPTIC HAND SANITIZER GEL, FRESH AIR

Active ingredient

Ethyl Alcohol 70% v/v

Purpose

Antiseptic

Uses

• hand sanitizer to decrease bacteria on the skin
• recommended for repeated use
• for use when soap and water are not available

Warnings

Flammable, keep away from fire/flame
For external use only

Do not use
• on children less than 2 months of age
• on open skin wounds

When using this product • do not get into eyes. In case of contact, rinse eyes thoroughly with water

Stop use and ask a doctor if
• irritation and redness develop
• condition persists for more than 72 hours

Keep out of reach of children. If swallowed, get medical help or contact a Poison Control Center right away.

Directions

• wet hands thoroughly with product and allow to dry without wiping
• supervise children under 6 years of age when using this product to avoid swallowing
• not recommended for infants

Other information

• store between 15-30°C (59-86°F)
• avoid freezing and excessive heat above 40°C (104°F).

Inactive ingredients

acrylates/vinyl isodecanoate cross-polymer, aminomethylpropanol, fragrance, glycerin, PEG-6, water

Questions? +1-206-505-3500

You may also report serious side effects to this phone number.
Mon-Fri 9:00 AM - 5:00 PM

Ethyl Alcohol 70% - Topical Gel

Fresh Air

MADE IN THE USA

WARNING
Extremely Flammable.
Keep away from flame

Distributed by:

TRINTERNATIONAL, INC.

600 Stewart Street, Suite 301

Seattle, WA 98101

WWW.TRICHEMICALS.COM

Infotrac 24-Hour Ph
+1 -800-535-5053 Acct #79932